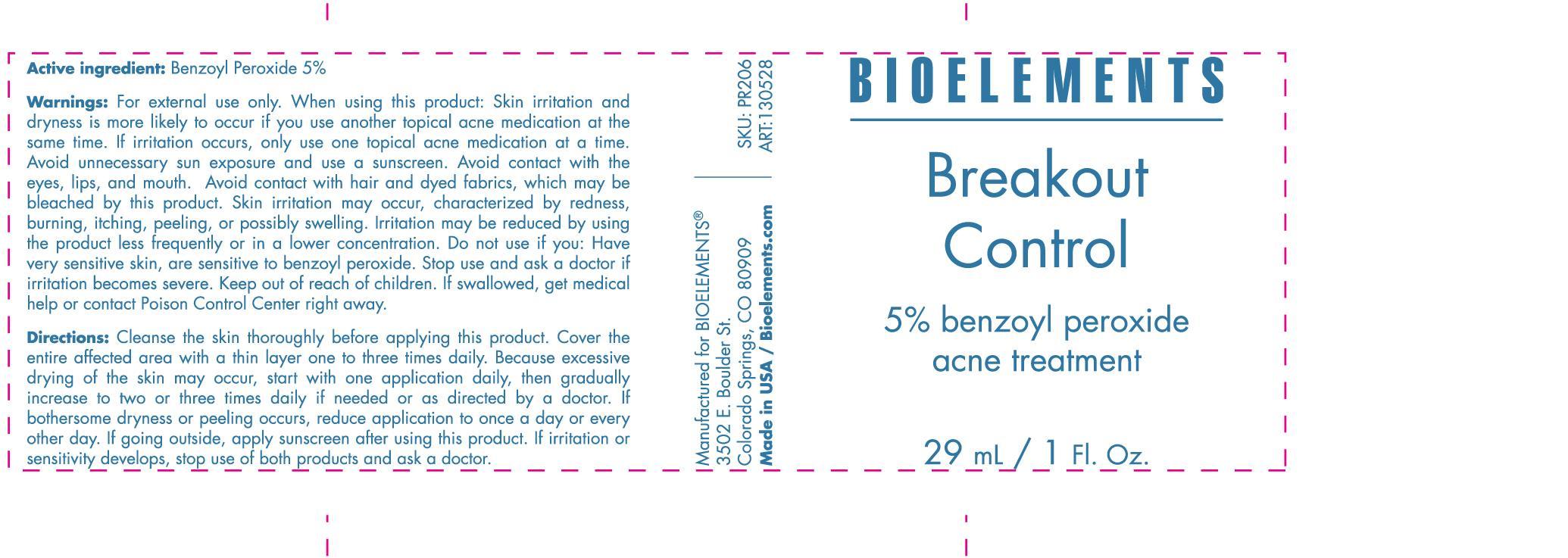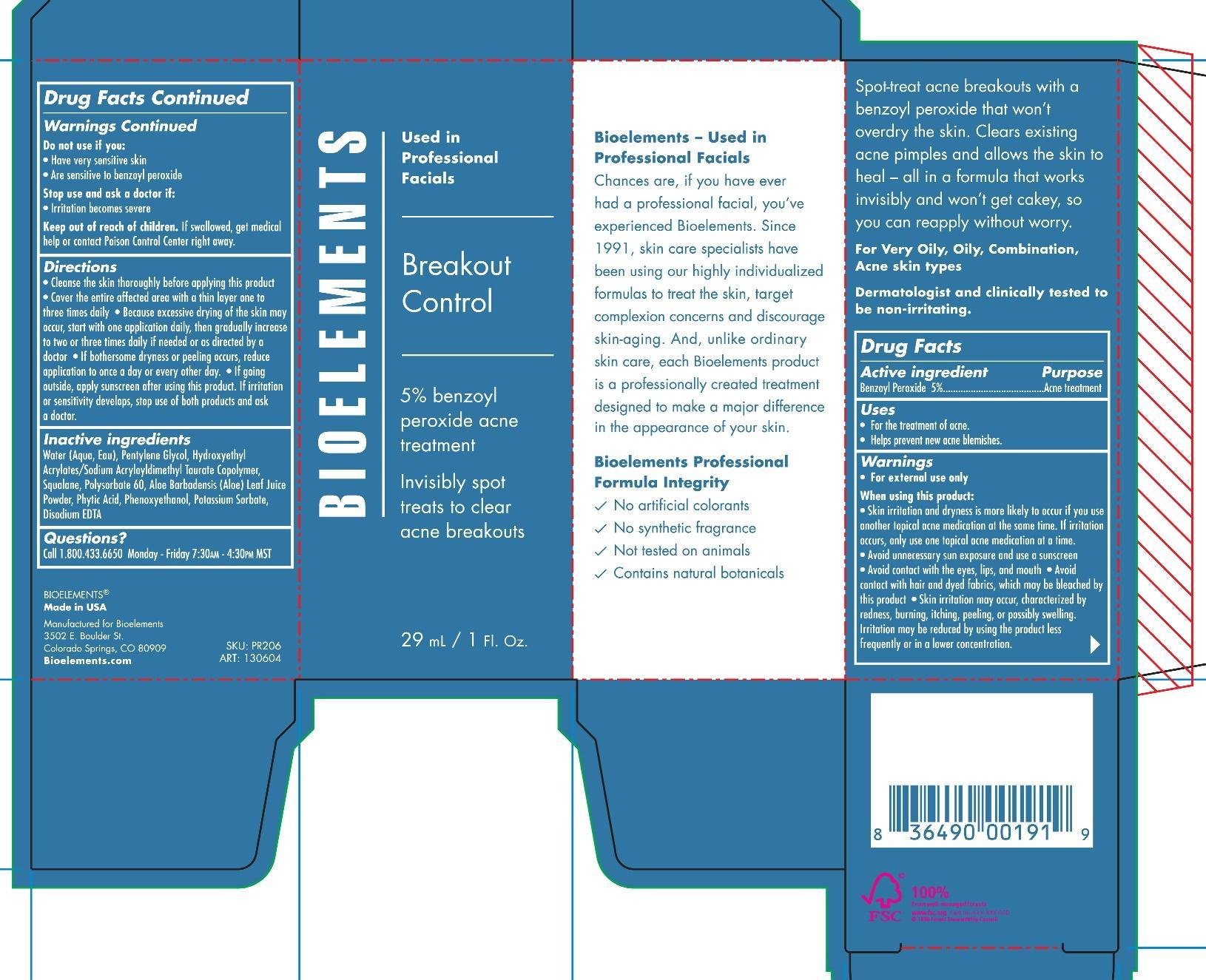 DRUG LABEL: Breakout Control
NDC: 56152-4009 | Form: CREAM
Manufacturer: Cosmetic Enterprises Ltd
Category: otc | Type: HUMAN OTC DRUG LABEL
Date: 20251010

ACTIVE INGREDIENTS: BENZOYL PEROXIDE 5 g/100 mL
INACTIVE INGREDIENTS: PENTYLENE GLYCOL; WATER; HYDROXYETHYL ACRYLATE/SODIUM ACRYLOYLDIMETHYL TAURATE COPOLYMER (45000 MPA.S AT 1%); SQUALANE; POLYSORBATE 60; FYTIC ACID; PHENOXYETHANOL; POTASSIUM SORBATE; EDETATE DISODIUM

Breakout Control

Active ingredient Purpose

Benzoyl Peroxide 5% Acne treatment

Uses

For the treatment of acne

Helps prevent new acne blemishes

Keep out of reach of children. If swallowed get medical help or contact Poison Control Center right away

Stop use and ask a doctor if:

irritation becomes severe

Warnings

For external use only

When using this product

- Skin irritation and dryness is more likely to occur if you use antoher topical acne medication at the same time. If irritation occurs only use only one topical acne medication at a time.

- Avoid unnecessary sun exposure and use a sunscreen

- Avoid contact with with the eyes lips and mouth

- Avoid contact with hair and dyed fabrics, which may be bleached by this product

- Skin irritation may occur, characterized by redness, burning, itching, peeling or possibly swelling . Irritation may be reduced by using the product less frequently or in a lower concentration.

- Do not use if you:

Have very sensitive skin

Are sensitive to benzoyl peroxide

Directions

Cleanse the skin thoroughly before applying this product

cover the entire with a thin layer one to three times daily

Because excessive drying of the skin may occur, start with one application daily then gradually increase to two or three times daily if needed or as directed by a doctor

If bothersome dryness or peeling occurs, reduce application to once a day or every other day

If going outside apply sunscreen after using this product. If irritation or sensitivity develops stop use of both products and ask a doctor.

Inactive ingredients

Water (Aqua,Eau), Pentylene Glycol, Hydroxyethyl Acrylates/Sodium Acryloyldimethyl Taurate Copolymer, Squalene, Polysorbate 60, Aloe Bardadensis (Aloe) Leaf Juice powder, Phytic Acid, Phyenoxyethanol, Potassium Sorbate, Disodium EDTA.

PACKAGE LABEL

Bioelements

Breakout control

5% benzoyl peroxide acne treatment

invisibly spot treats to clear acne breakouts

29 mL/ 1 Fl. Oz.